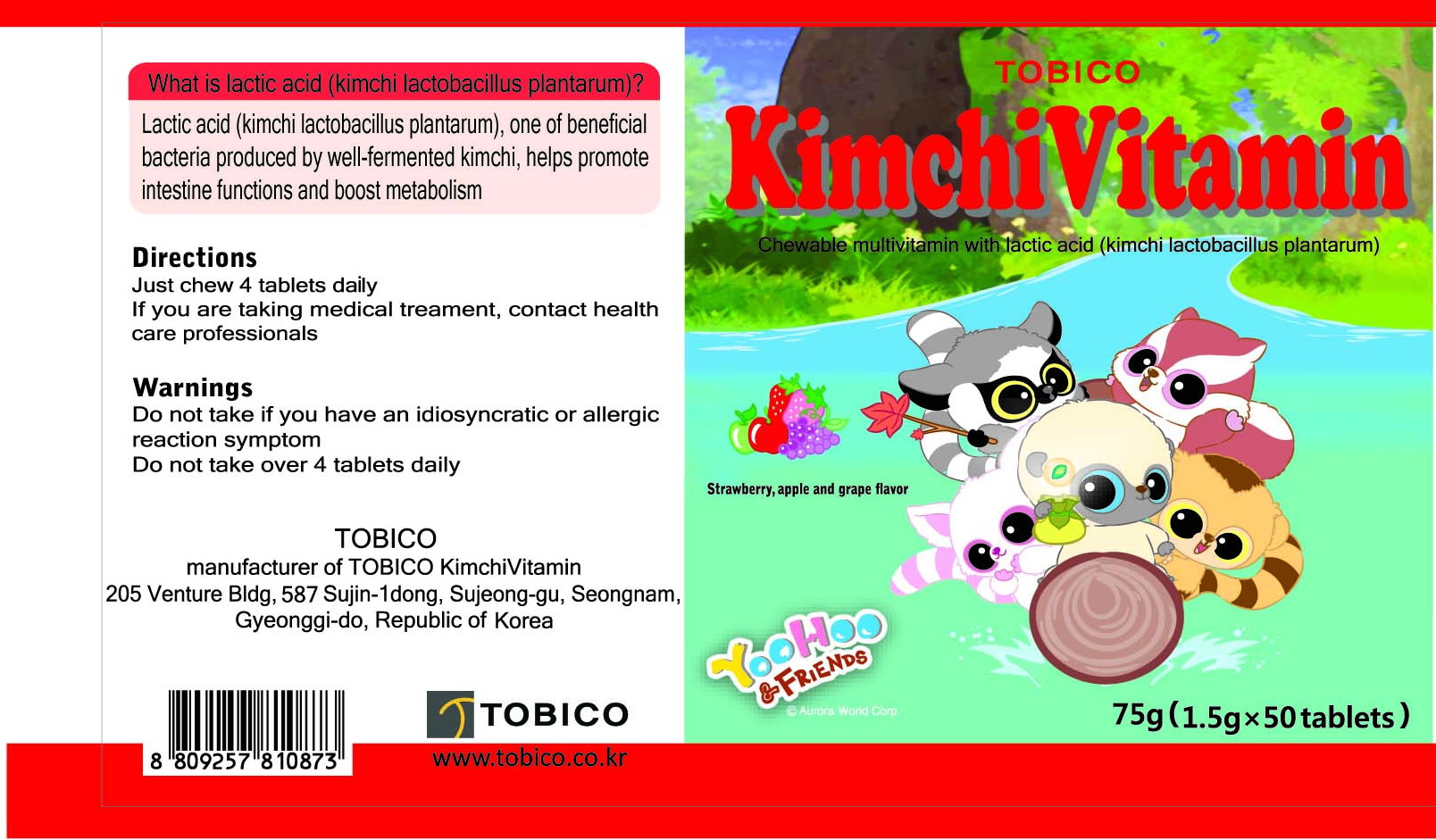 DRUG LABEL: Kimchi Vitamin
NDC: 52102-1001 | Form: TABLET, CHEWABLE
Manufacturer: Tobico
Category: otc | Type: HUMAN OTC DRUG LABEL
Date: 20100318

ACTIVE INGREDIENTS: LACTIC ACID 30 mg/1 1; ASCORBIC ACID 180 mg/1 1; THIAMINE 0.195 mg/1 1; PYRIDOXINE 0.285 mg/1 1; VITAMIN A 0.675 mg/1 1; ALPHA-TOCOPHEROL 1.875 mg/1 1; FOLIC ACID 0.03 mg/1 1; COLLAGENASE 5.625 mg/1 1; RIBOFLAVIN 0.24 mg/1 1; CHOLECALCIFEROL 0.375 mg/1 1; NIACINAMIDE 0.045 mg/1 1

Drug Facts

Active Ingredient: lactic acid, ascorbic acid, pyridoxin, Vitamin A, alpha-tocopherol, folic acid, collagen, riboflavin, cholecalciferol, niacinamide, thiamine mononitrate

Uses
■ Daily nutrient supplement and maintenance of healthy intestine
Warnings
■ Do not take if you have an idiosyncratic or allergic reaction symptom
■ Do not take over 4 tablets daily
Directions
■ Just chew 4 tablets daily
■ If you are taking medical treatment, contact health care professionals
Other information
■ Store at room temperature and keep out of direct sunlight
■ Keep bottle tightly closed
■ Keep out of reach of the children
■ Keep seal for freshness